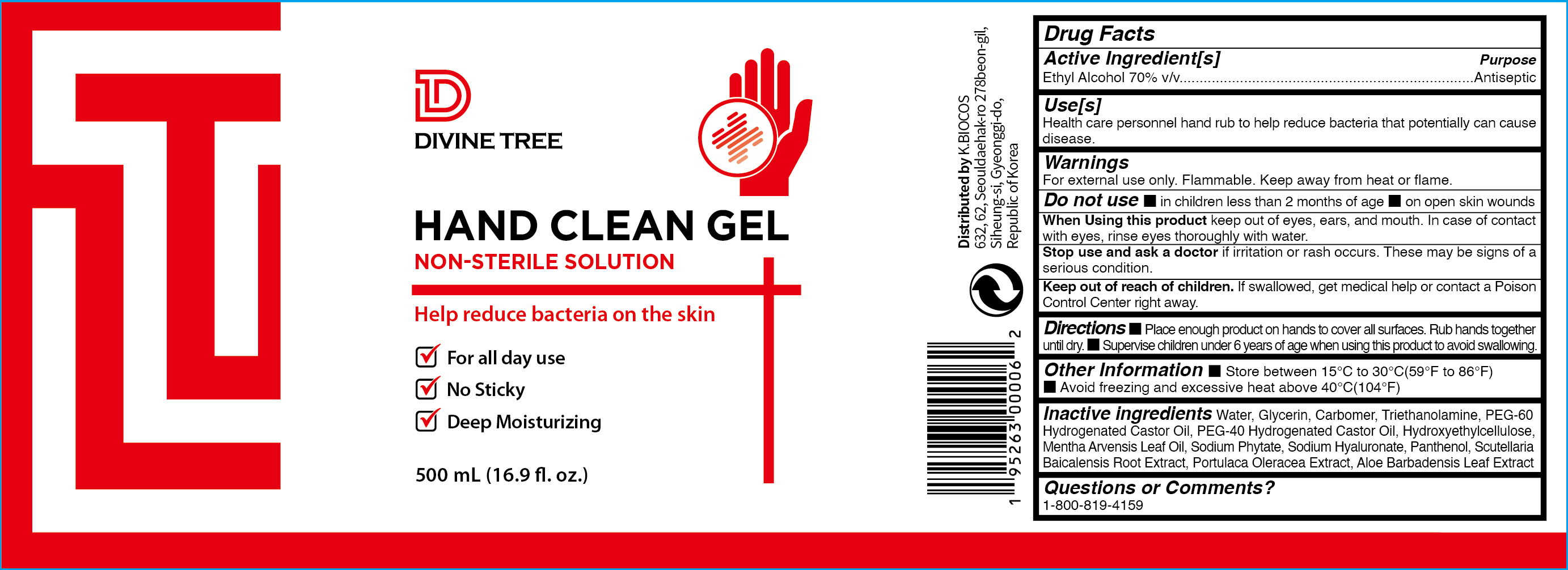 DRUG LABEL: Divine Tree Hand Clean Gel 500ml
NDC: 73494-502 | Form: LIQUID
Manufacturer: K.BIOCOS
Category: otc | Type: HUMAN OTC DRUG LABEL
Date: 20200525

ACTIVE INGREDIENTS: ALCOHOL 70 mL/100 mL
INACTIVE INGREDIENTS: AMINOMETHYLPROPANOL; HYALURONATE SODIUM; .ALPHA.-TOCOPHEROL ACETATE; GLYCERIN; CARBOMER 940; ALOE VERA LEAF; WATER; MENTHA ARVENSIS LEAF OIL; PANTHENOL

Divine Tree Hand Clean Gel 500ml

Active Ingredient

Active Ingredient-Ethyl Alcohol 70% v/v.

Purpose

Purpose-Antiseptic

Use(s)

Use(s) Hand Sanitizer to help reduce bacteria that potentially can cause disease. For use when soap and water are not available.

Warnings

Warnings-For external use only. Flammable. Keep away from heat or flame

Do Not Use

▪in children less than 2 months of age
▪on open skin wounds

When Using this product- keep out of eyes, ears, and mouth. In case of contact with eyes, rinse eyes thoroughly with water.

Stop Use and ask a doctor-if irritation or rash occurs. These may be signs of a serious condition.

Keep out of reach of children If swallowed, get medical help or contact a Poison Control Center right away.

Directions

Directions • Place enough product on hands to cover all surfaces. Rub hands together until dry.
• Supervise children under 6 years of age when using this product to avoid swallowing.

Other Information

▪ Store between 15-30C (59-86F)
▪ Avoid freezing and excessive heat above 40C (104F)

Inactive Ingredients

Inactive Ingredients-Water, Glycerin, Carbomer, Triethanolamine, PEG-60 Hydrogenated Castor Oil, PEG-40 Hydrogenated Castor Oil, Hydroxyethylcellulose, Mentha Arvensis Leaf Oil, Sodium Phytate, Sodium Hyaluronate, Panthenol
Scutellaria Baicalensis Root Extract, Portulaca Oleracea Extract, Aloe Barbadensis Leaf Extract

Questions or Comments-1-800-819-4159

Principal Display Panel